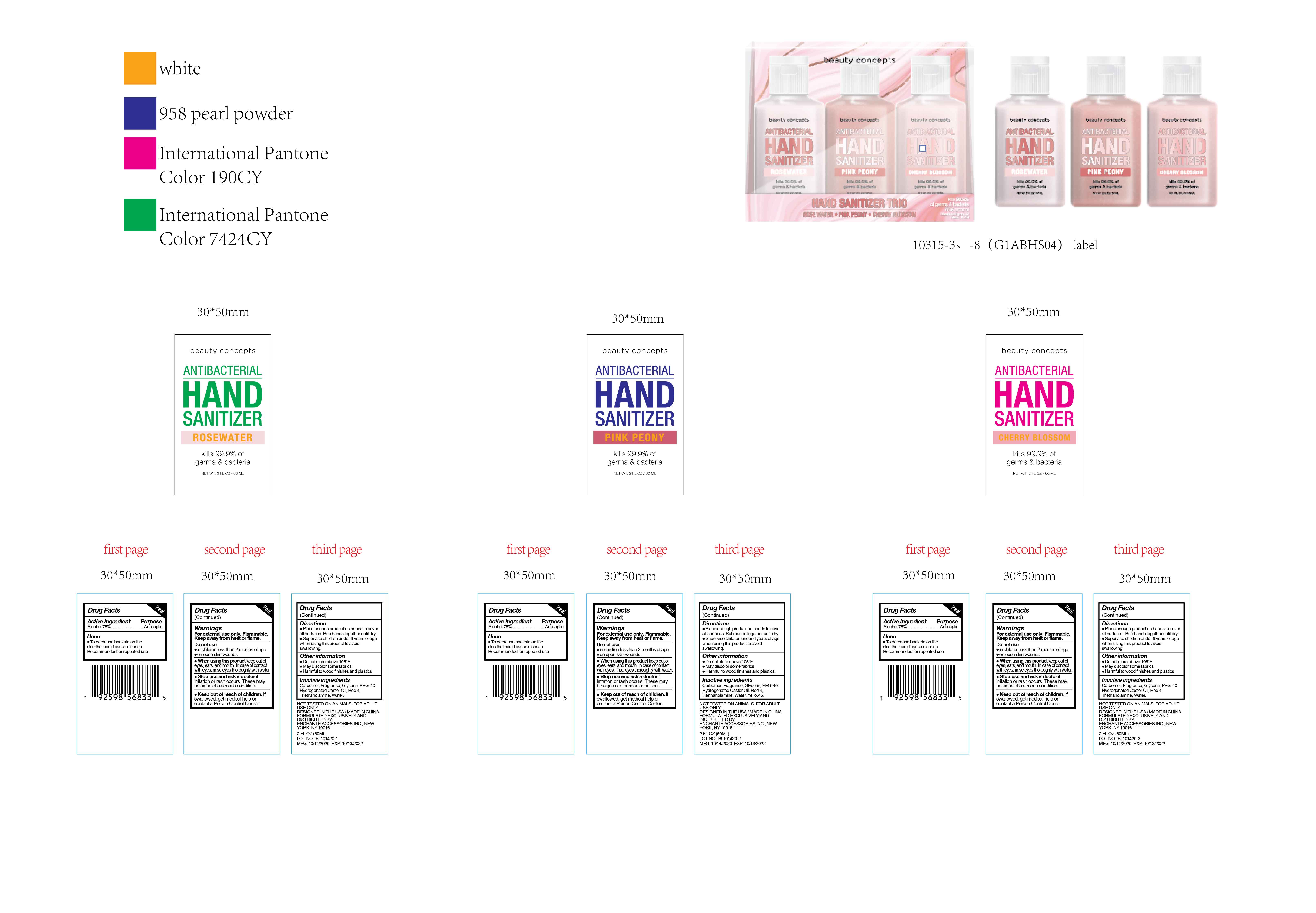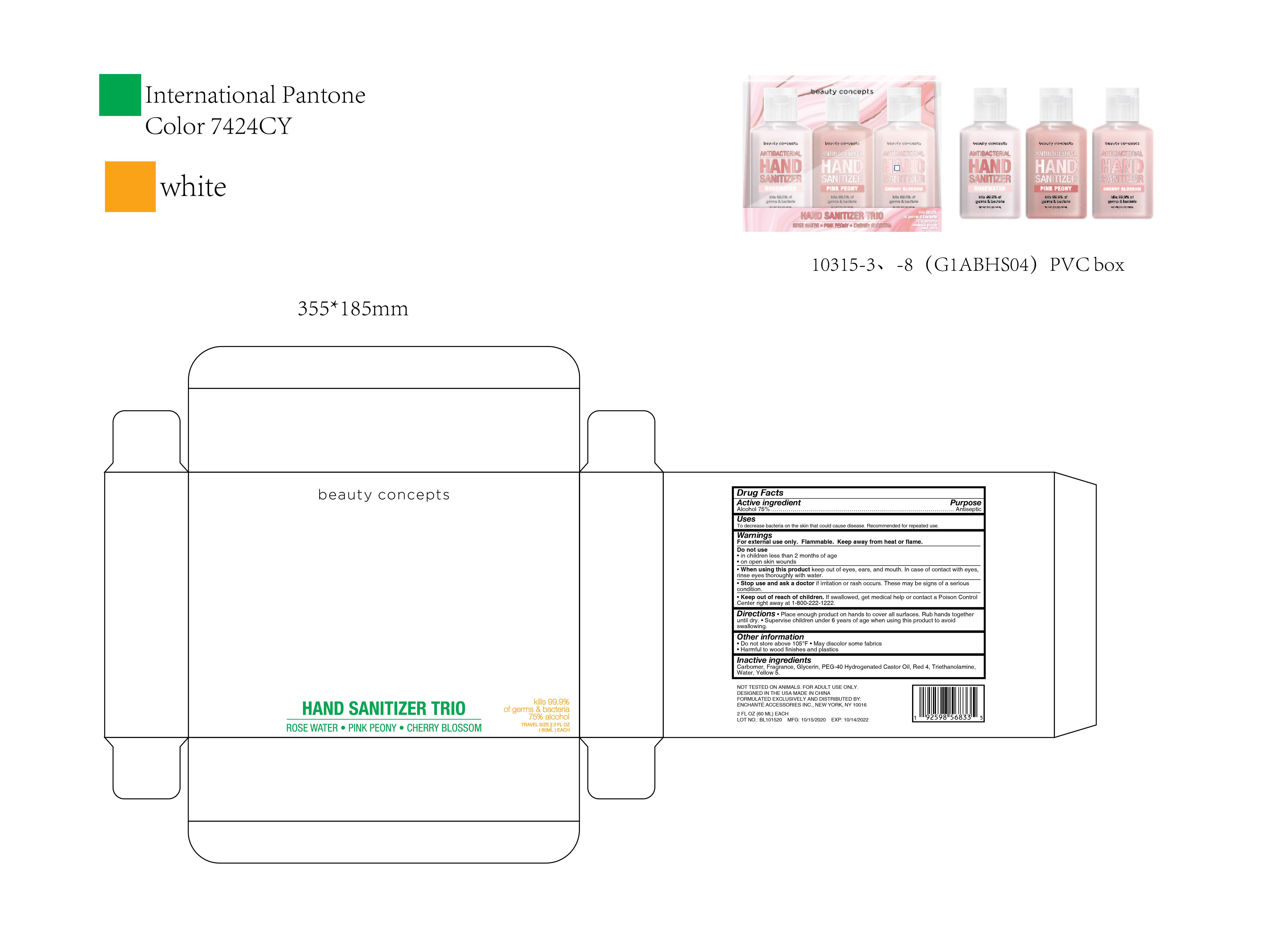 DRUG LABEL: beauty concepts HAND SANITIZER TRIO ROSE WATER PINK PEONY CHERRY BLOSSOM
NDC: 50563-390 | Form: KIT | Route: TOPICAL
Manufacturer: ENCHANTE ACCESSORIES INC.
Category: otc | Type: HUMAN OTC DRUG LABEL
Date: 20201101

ACTIVE INGREDIENTS: ALCOHOL 75 mL/100 mL; ALCOHOL 75 mL/100 mL; ALCOHOL 75 mL/100 mL
INACTIVE INGREDIENTS: WATER; GLYCERIN; CARBOMER 940; TROLAMINE; POLYOXYL 40 HYDROGENATED CASTOR OIL; FD&C RED NO. 4; WATER; GLYCERIN; CARBOMER 940; TROLAMINE; POLYOXYL 40 HYDROGENATED CASTOR OIL; FD&C RED NO. 4; FD&C YELLOW NO. 5; WATER; GLYCERIN; CARBOMER 940; TROLAMINE; POLYOXYL 40 HYDROGENATED CASTOR OIL; FD&C RED NO. 4

50563_387/388/389/390_G1ABHS04

beauty concepts ANTIBACTERIAL HAND SANITIZER ROSE WATER

Active Ingredient

Alcohol 75%

Purpose

Antiseptic

Use

■ To decrease bacteria on the skin that could cause disease
■Recommended for repeated use

WARNINGS

For external use only

Flammable. Keep away from heat or flame

When using this product, keep out of eyes, ears, and mouth
In case of contact with eyes, rinse eyes thoroughly with water

Do not use

- in children less than 2 months of age
- on open skin wounds

Stop use and ask a doctor if irritation or rash occurs. These may be signs of a serious condition

Keep out of reach of children. If swallowed, get medical help or contact a Poison Control Center.

Directions

Place enough product on hands to cover all surfaces. Rub hands together until dry.

Supervise children under 6 years of age when using this product to avoid swallowing

Other information

Do not store above 105F

May discolor some fabrics

Harmful to wood finishes and plastics

Inactive ingredients

Carbomer, Glycerin, PEG-40 Hydrogenated Castor Oil, Red 4, Triethanolamine, Water

beauty concepts ANTIBACTERIAL HAND SANITIZER PINK PEONY

Active Ingredient

Alcohol 75%

Purpose

Antiseptic

Uses

- To decrease bacteria on the skin that could cause disease

■Recommended for repeated use

Warnings

For external use only

Flammable. Keep away from heat or flame

When using this product, keep out of eyes, ears, and mouth
In case of contact with eyes, rinse eyes thoroughly with water

Do not use

- in children less than two months of age
- on open skin wounds

Stop use and ask a doctor if irritation or rash occurs. These may be signs of a serious condition

Keep out of reach of children. If swallowed, get medical help or contact a Poison Control Center.

Directions

Place enough product on hands to cover all surfaces. Rub hands together until dry.

Supervise children under 6 years of age when using this product to avoid swallowing

Other Information

Do not store above 105F

May discolor some fabrics

Harmful to wood finishes and plastics

Inactive Ingredients

Carbomer, Glycerin, PEG-40 Hydrogenated Castor Oil, Red 4, Triethanolamine, Water, Yellow 5

beauty concepts ANTIBACTERIAL HAND SANITIZER CHERRY BLOSSOM

Active Ingredient

Alcohol 75%

Purpose

Antiseptic

Uses

- To decrease bacteria on the skin that could cause disease

■Recommended for repeated use

Warnings

For external use only

Flammable. Keep away from heat or flame

When using this product, keep out of eyes, ears, and mouth
In case of contact with eyes, rinse eyes thoroughly with water

Do not use

- in children less than 2 months of age
- on open skin wounds

Stop use and ask a doctor if irritation or rash occurs. These may be signs of a serious condition

Keep out of reach of children. If swallowed, get medical help or contact a Poison Control Center.

Directions

Place enough product on hands to cover all surfaces. Rub hands together until dry.

Supervise children under 6 years of age when using this product to avoid swallowing

Other Information

Do not store above 105F

May discolor some fabrics

Harmful to wood finishes and plastics

Inactive Ingredients

Carbomer, Glycerin, PEG-40 Hydrogenated Castor Oil, Red 4, Triethanolamine, Water